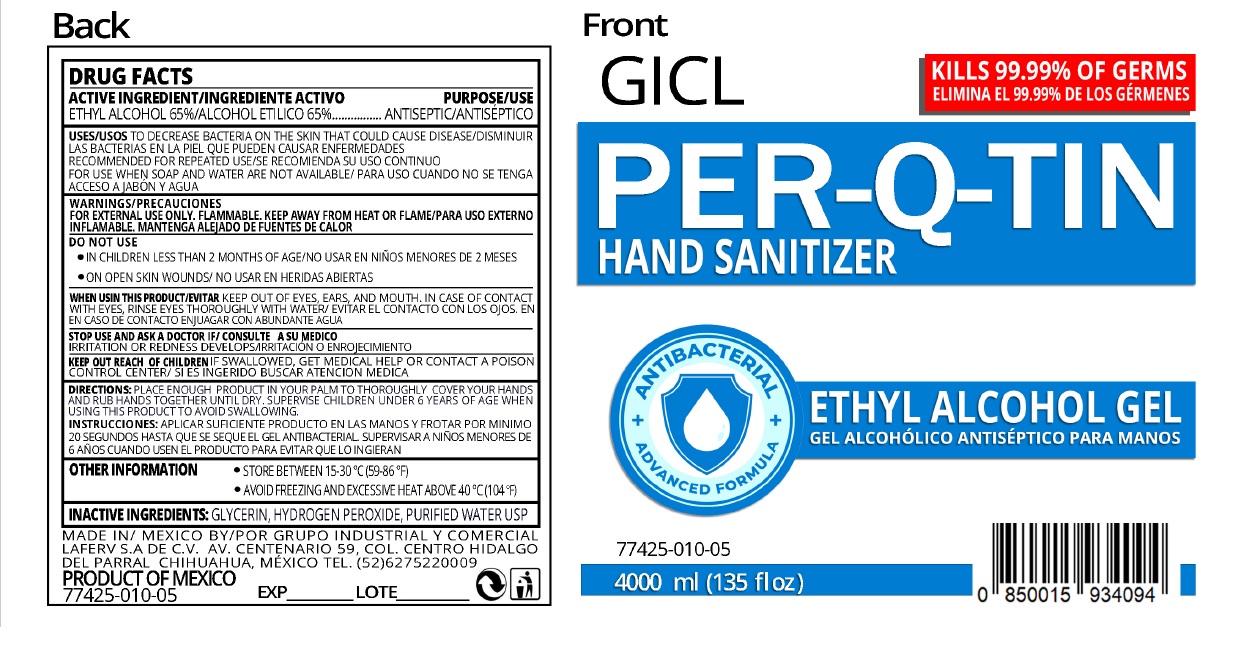 DRUG LABEL: PERQTIN HAND SANITIZER
NDC: 77425-010 | Form: GEL
Manufacturer: Grupo Industrial Y Comercial Laferv, S.a. De C.v.
Category: otc | Type: HUMAN OTC DRUG LABEL
Date: 20200506

ACTIVE INGREDIENTS: ALCOHOL 65 mL/100 mL
INACTIVE INGREDIENTS: GLYCERIN; HYDROGEN PEROXIDE; WATER

GICL PER-Q-TIN HAND SANITIZER GEL

ACTIVE INGREDIENT

ETHYL ALCOHOL 65%

PURPOSE

ANTISEPTIC

INDICATIONS AND USAGE

USES TO DECREASE BACTERIA ON THE SKIN THAT COULD CAUSE DISEASE

RECOMMENDED FOR REPEATED USE

FOR USE WHEN SOAP AND WATER ARE NOT AVAILABLE

WARNINGS

FOR EXTERNAL USE ONLY. FLAMMABLE. KEEP AWAY FROM HEAT OR FLAME

DO NOT USE

• IN CHILDREN LESS THAN 2 MONTHS OF AGE

• ON OPEN SKIN WOUNDS

WHEN USING THIS PRODUCT KEEP OUT OF EYES, EARS, AND MOUTH. IN CASE OF CONTACT WITH EYES, RINSE EYES THOROUGHLY WITH WATER

STOP USE AND ASK A DOCTOR IF IRRITATION OR REDNESS DEVELOPS

KEEP OUT OF REACH OF CHILDREN IF SWALLOWED, GET MEDICAL HELP OR CONTACT A POISON CONTROL CENTER

DOSAGE AND ADMINISTRATION

DIRECTIONS: PLACE ENOUGH PRODUCT IN YOUR PALM TO THOROUGHLY COVER YOUR HANDS AND RUB HANDS TOGETHER UNTIL DRY. SUPERVISE CHILDREN UNDER 6 YEARS OF AGE WHEN USING THIS PRODUCT TO AVOID SWALLOWING.

OTHER INFORMATION • STORE BETWEEN 15-30°C (59-86°F)

• AVOID FREEZING AND EXCESSIVE HEAT ABOVE 40°C (104°F)

INACTIVE INGREDIENTS: GLYCERIN, HYDROGEN PEROXIDE, PURIFIED WATER USP

KILLS 99.99% OF GERMS

70% ETHYL ALCOHOL

ANTIBACTERIAL

ADVANCED FORMULA

MADE IN MEXICO BY GRUPO INDUSTRIAL Y COMERCIAL LAFERV S.A DE C.V. AV. CENTENARIO 59, COL. CENTRO HIDALGO DEL PARRAL CHIHUAHUA, MEXICO TEL. (52)6275220009

PRODUCT OF MEXICO